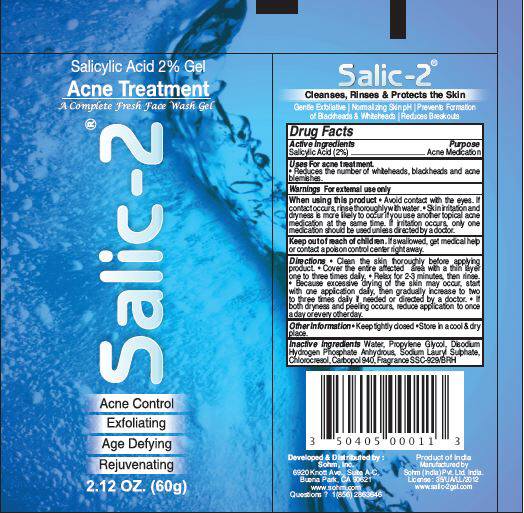 DRUG LABEL: Salic-2
NDC: 50405-110 | Form: GEL
Manufacturer: SOHM Inc.
Category: otc | Type: HUMAN OTC DRUG LABEL
Date: 20131111

ACTIVE INGREDIENTS: Salicylic Acid 1.2 g/60 g
INACTIVE INGREDIENTS: Propylene Glycol; Sodium Phosphate, Dibasic, Anhydrous; Sodium Lauryl Sulfate; Chlorocresol; Carbomer Homopolymer Type C (Allyl Pentaerythritol Crosslinked); Water

Salic-2®

Drug Facts

Active ingredients

Salicylic Acid (2%)

Purpose

Acne Medication

Uses For acne treatment

- Reduces the number of whiteheads, blackheads and acne blemishes.

Warnings

For external use only

When using this product

- Avoid contact with the eyes. If contact occurs, rinse thoroughly with water.
- Skin irritation and dryness is more likely to occur if you use another topical acne medication at the same time. If irritation occurs, only one medication should be used unless directed by a doctor.

Keep out of reach of children. If swallowed, get medical help or contact a poison control center right away.

Directions

- Clean the skin thoroughly before applying product.
- Cover the entire affected area with a thin layer one to three times daily.
- Relax for 2-3 minutes, then rinse.
- Because excessive drying of the skin may occur, start with one application daily, then gradually increase to two to three times daily if needed or directed by a doctor.
- If both dryness and peeling occurs, reduce application to once a day or every other day.

Other information

- Keep tightly closed
- Store in a cool & dry place.

Inactive ingredients

Water, Propylene Glycol, Disodium Hydrogen Phosphate Anhydrous, Sodium Lauryl Sulphate, Chlorocresol, Carbopol 940, Fragrance SSC-929/BRH

Questions ?

1(856) 2863646

Distributed by :
Sohm, Inc.
6920 Knott Ave., Suite A-C
Buena Park, CA 90621

Manufactured by
Sohm (India) Pvt. Ltd. India.

PRINCIPAL DISPLAY PANEL - 60g Tube Label

Salicylic Acid 2% Gel

Acne Treatment
A Complete Fresh Face Wash Gel

Salic-2®

Acne Control

Exfoliating

Age Defying

Rejuvenating

2.12 OZ 60g)